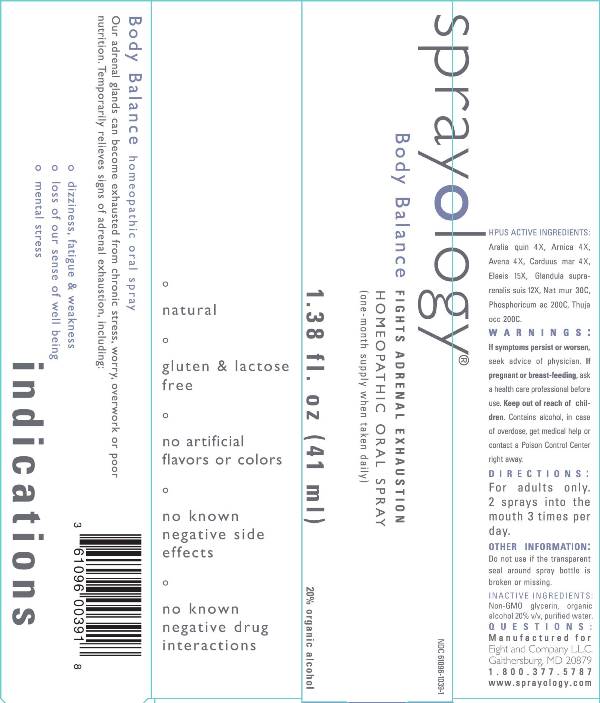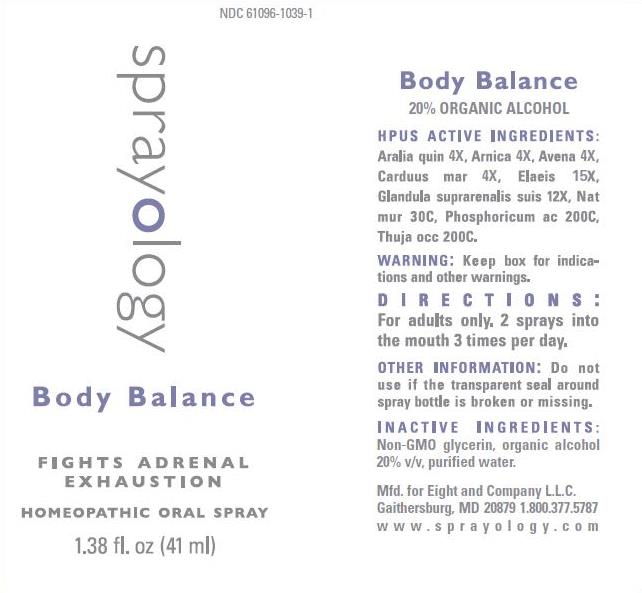 DRUG LABEL: Body Balance
NDC: 61096-1039 | Form: LIQUID
Manufacturer: Eight and Company L.L.C
Category: homeopathic | Type: HUMAN OTC DRUG LABEL
Date: 20251218

ACTIVE INGREDIENTS: AMERICAN GINSENG 4 [hp_X]/41 mL; ARNICA MONTANA WHOLE 4 [hp_X]/41 mL; AVENA SATIVA FLOWERING TOP 4 [hp_X]/41 mL; MILK THISTLE 4 [hp_X]/41 mL; ELAEIS GUINEENSIS FRUIT 15 [hp_X]/41 mL; SUS SCROFA ADRENAL GLAND 12 [hp_X]/41 mL; SODIUM CHLORIDE 30 [hp_C]/41 mL; PHOSPHORIC ACID 200 [hp_C]/41 mL; THUJA OCCIDENTALIS LEAFY TWIG 200 [hp_C]/41 mL
INACTIVE INGREDIENTS: GLYCERIN; ALCOHOL; WATER

Body Balance

ACTIVE INGREDIENTS:

Aralia quin 4X, Arnica 4X, Avena sativa 4X, Carduus mar 4X, Elaeis 15X, Glandula suprarenalis suis 12X, Nat mur 30C, Phosphoricum acidum 200C, Thuja occ 200C.

PURPOSE:

Our adrenal glands can become exhausted from chronic stress, worry, overwork or poor nutrition. Temporarily relieves signs of adrenal exhaustion, including:

° dizziness, fatigue & weakness
° loss of sense of well being
° mental stress

WARNINGS:

If symptoms persist or worsen, seek advice of physician. If pregnant or breast-feeding, ask a health care professional before use. Keep out of reach of children. Contains alcohol, in case of overdose, get medical help or contact a Poison Control Center right away.

Keep out of reach of children. Contains alcohol, in case of overdose, get medical help or contact a Poison Control Center right away.

DIRECTIONS:

For adults only. 2 sprays into the mouth 3 times per day.

OTHER INFORMATION:

Do not use if the transparent seal around spray bottle is broken or missing.

INDICATIONS:

Our adrenal glands can become exhausted from chronic stress, worry, overwork or poor nutrition. Temporarily relieves signs of adrenal exhaustion, including:

° dizziness fatigue & weakness

° mental stress

° loss of our sense of well being

° natural

° gluten & lactose free

° no artificial flavors or colors

° no known negative side effects

° no known negative drug interactions

INACTIVE INGREDIENTS:

Non-GMO glycerin, organic alcohol 20% v/v, purified water.

QUESTIONS:

Mfd. for Eight and Company L.L.C.

Gaithersburg, MD 20879 1.800.377.5787

www.sprayology.com

PACKAGE LABEL DISPLAY:

NDC 61096-1039-1

sprayology

Body Balance

FIGHTS ADRENAL EXHAUSTION

HOMEOPATHIC ORAL SPRAY

1.38 fl.oz (41 ml)